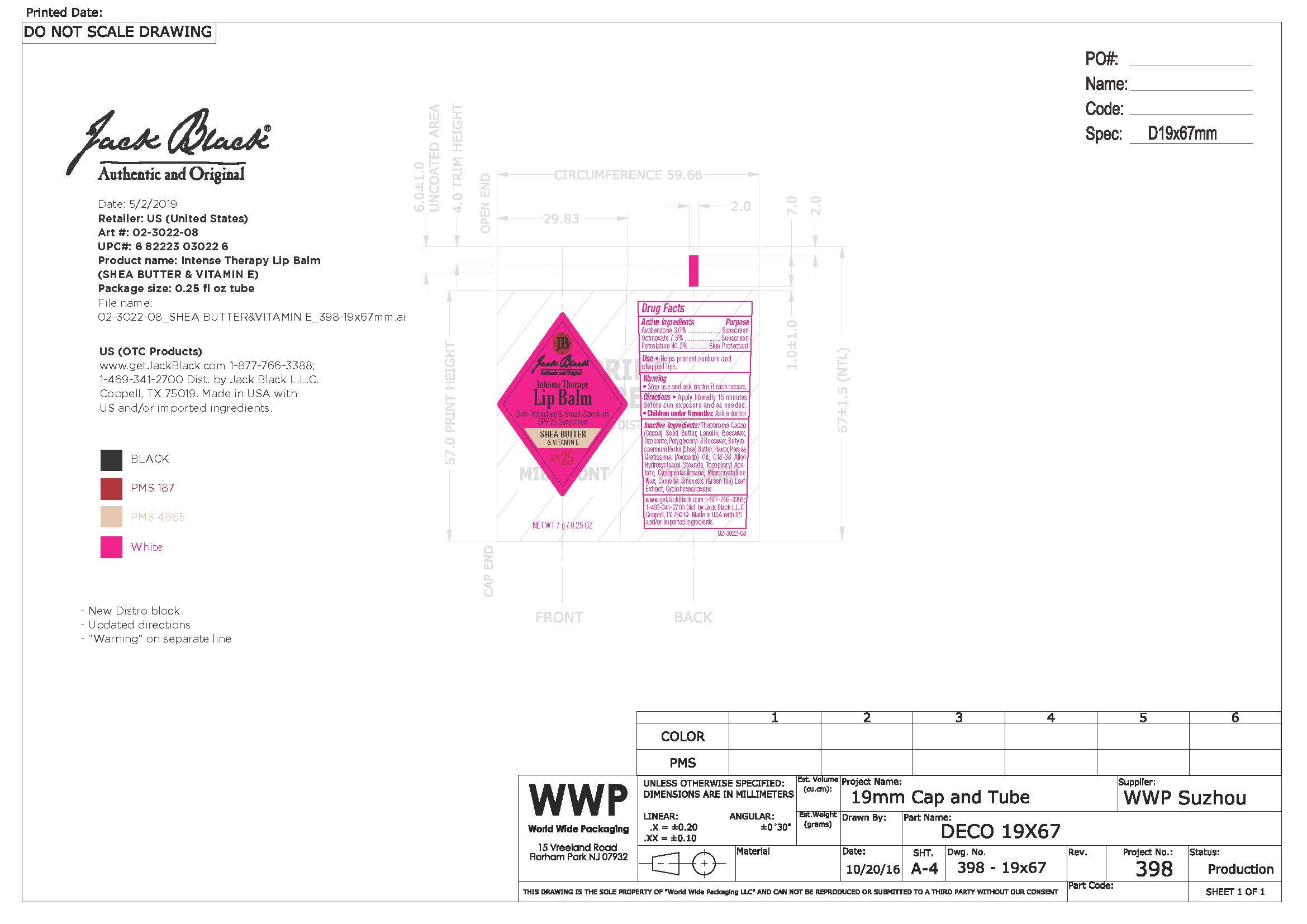 DRUG LABEL: Intense Therapy Lip Balm SPF25, Shea Butter and Vitamin E
NDC: 66738-030 | Form: OINTMENT
Manufacturer: Jack Black, LLC
Category: otc | Type: HUMAN OTC DRUG LABEL
Date: 20231109

ACTIVE INGREDIENTS: AVOBENZONE 3 g/1000 g; OCTINOXATE 7.5 g/1000 g; PETROLATUM 40.2 g/1000 g
INACTIVE INGREDIENTS: WHITE WAX; SHEA BUTTER; GREEN TEA LEAF; CYCLOMETHICONE 6; CYCLOMETHICONE 5; LANOLIN OIL; MICROCRYSTALLINE WAX; AVOCADO OIL; CERESIN; COCOA BUTTER; .ALPHA.-TOCOPHEROL ACETATE

Jack Black Intense Therapy Lip Balm SPF25, Shea Butter & Vitamin E

Active Ingredients

Avobenzone 3.0% Sunscreen

Octinoxate 7.5% Sunscreen

Petrolatum 40.2% Skin Protectant

Use

Helps prevent sunburn and chapped lips

Warning

Stop use if skin rash occurs

Directions

Apply liberally 15 minutes before sun exposure and as needed. Children under 6 monhts: ask a doctor.

Inactive Ingredients

Beeswax, Butyrospermum parkii (Shea) Butter, C 18-38 Alkyl Hydroxystearoyl Stearate, Camellia Sinensis (Green tea) Leaf Extract, Cyclohexasiloxane, Cyclopentasiloxane, Flavor, Lanolin, Microcyrstalline Wax, Ozokerite, Persea gratissima (avocado) oil, Polyglyceryl-3 Beeswax, Theobroma cacao (cocoa) See Butter, Tocopheryl Acetate

KEEP OUT OF REACH OF CHILDREN

Questions

1-877-766-3388

www.getjackblack.com